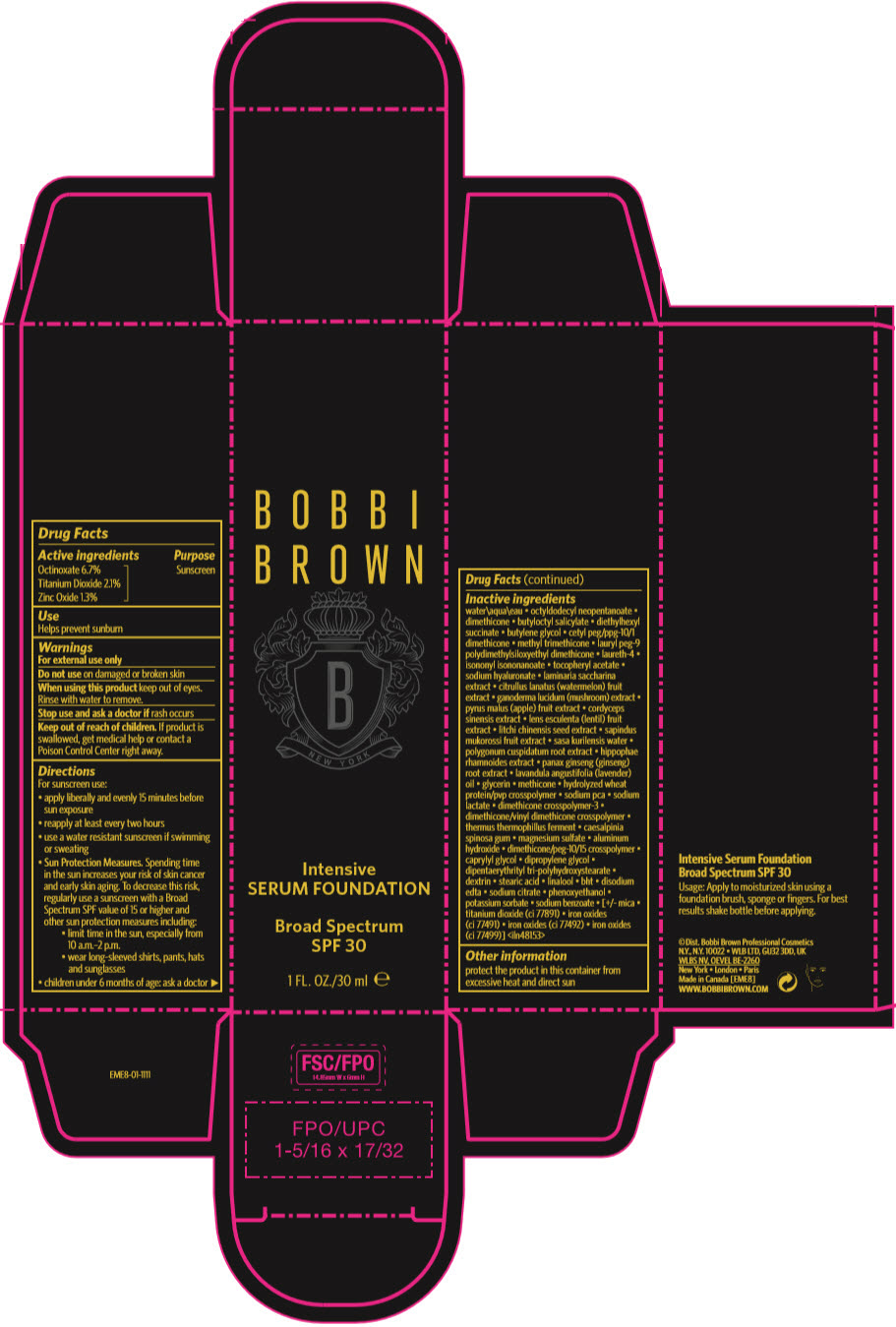 DRUG LABEL: BOBBI BROWN INTENSIVE SERUM FOUNDATION BROAD SPECTRUM SPF 30
NDC: 64141-032 | Form: LIQUID
Manufacturer: Bobbi Brown Professional Cosmetics Inc.
Category: otc | Type: HUMAN OTC DRUG LABEL
Date: 20241216

ACTIVE INGREDIENTS: OCTINOXATE 67 mg/1 mL; TITANIUM DIOXIDE 21 mg/1 mL; ZINC OXIDE 13 mg/1 mL
INACTIVE INGREDIENTS: DIPROPYLENE GLYCOL; DIPENTAERYTHRITYL TRI-POLYHYDROXYSTEARATE; DEXTRIN PALMITATE (CORN; 20000 MW); STEARIC ACID; LINALOOL, (+)-; BUTYLATED HYDROXYTOLUENE; DISODIUM ZINC EDETATE; SODIUM CITRATE, UNSPECIFIED FORM; PHENOXYETHANOL; POTASSIUM SORBATE; SODIUM BENZOATE; MICA; FERRIC OXIDE RED; FERRIC OXIDE YELLOW; FERROSOFERRIC OXIDE; WATER; OCTYLDODECYL NEOPENTANOATE; DIMETHICONE; BUTYLOCTYL SALICYLATE; DIETHYLHEXYL SUCCINATE; BUTYLENE GLYCOL; CETYL PEG/PPG-10/1 DIMETHICONE (HLB 2); METHYL TRIMETHICONE; LAURYL PEG-9 POLYDIMETHYLSILOXYETHYL DIMETHICONE; LAURETH-4; ISONONYL ISONONANOATE; .ALPHA.-TOCOPHEROL ACETATE; HYALURONATE SODIUM; SACCHARINA LATISSIMA; WATERMELON; REISHI; APPLE; OPHIOCORDYCEPS SINENSIS; LENS CULINARIS FRUIT; LITCHI CHINENSIS SEED; SAPINDUS MUKOROSSI FRUIT; SASA KURILENSIS WHOLE; REYNOUTRIA JAPONICA ROOT; HIPPOPHAE RHAMNOIDES FRUIT; PANAX GINSENG ROOT OIL; LAVENDER OIL; GLYCERIN; METHICONE (20 CST); HYDROLYZED WHEAT PROTEIN (ENZYMATIC; 3000 MW); SODIUM PYRROLIDONE CARBOXYLATE; SODIUM LACTATE; DIMETHICONE CROSSPOLYMER (450000 MPA.S AT 12% IN CYCLOPENTASILOXANE); DIMETHICONE/VINYL DIMETHICONE CROSSPOLYMER (HARD PARTICLE); THERMUS THERMOPHILUS; CAESALPINIA SPINOSA RESIN; MAGNESIUM SULFATE, UNSPECIFIED FORM; ALUMINUM HYDROXIDE; DIMETHICONE/PEG-10/15 CROSSPOLYMER; CAPRYLYL GLYCOL

BOBBI BROWN INTENSIVE SERUM FOUNDATION BROAD SPECTRUM SPF 30

Drug Facts

Active ingredients

Octinoxate 6.7%
Titanium Dioxide 2.1%
Zinc Oxide 1.3%

Purpose

Sunscreen

Use

Helps prevent sunburn

Warnings

For external use only

Do not use on damaged or broken skin

When using this product keep out of eyes.

Rinse with water to remove.

Stop use and ask a doctor if rash occurs

Keep out of reach of children. If product is swallowed, get medical help or contact a Poison Control Center right away.

Directions

For sunscreen use:

- apply liberally and evenly 15 minutes before sun exposure
- reapply at least every two hours
- use a water resistant sunscreen if swimming or sweating
- Sun Protection Measures. Spending time in the sun increases your risk of skin cancer and early skin aging. To decrease this risk, regularly use a sunscreen with a Broad Spectrum SPF value of 15 or higher and other sun protection measures including:
  - limit time in the sun, especially from 10 a.m.–2 p.m.
  - wear long-sleeved shirts, pants, hats and sunglasses
- children under 6 months of age: ask a doctor

Inactive ingredients

water\aqua\eau • octyldodecyl neopentanoate • dimethicone • butyloctyl salicylate • diethylhexyl succinate • butylene glycol • cetyl peg/ppg-10/1 dimethicone • methyl trimethicone • lauryl peg-9 polydimethylsiloxyethyl dimethicone • laureth-4 • isononyl isononanoate • tocopheryl acetate • sodium hyaluronate • laminaria saccharina extract • citrullus lanatus (watermelon) fruit extract • ganoderma lucidum (mushroom) extract • pyrus malus (apple) fruit extract • cordyceps sinensis extract • lens esculenta (lentil) fruit extract • litchi chinensis seed extract • sapindus mukorossi fruit extract • sasa kurilensis water • polygonum cuspidatum root extract • hippophae rhamnoides extract • panax ginseng (ginseng) root extract • lavandula angustifolia (lavender) oil • glycerin • methicone • hydrolyzed wheat protein/pvp crosspolymer • sodium pca • sodium lactate • dimethicone crosspolymer-3 • dimethicone/vinyl dimethicone crosspolymer • thermus thermophillus ferment • caesalpinia spinosa gum • magnesium sulfate • aluminum hydroxide • dimethicone/peg-10/15 crosspolymer • caprylyl glycol • dipropylene glycol • dipentaerythrityl tri-polyhydroxystearate • dextrin • stearic acid • linalool • bht • disodium edta • sodium citrate • phenoxyethanol • potassium sorbate • sodium benzoate • [+/- mica • titanium dioxide (ci 77891) • iron oxides (ci 77491) • iron oxides (ci 77492) • iron oxides (ci 77499)] <iln48153>

Other information

protect the product in this container from excessive heat and direct sun

PRINCIPAL DISPLAY PANEL - 30 ml Bottle Carton

BOBBI
BROWN

Intensive
SERUM FOUNDATION

Broad Spectrum
SPF 30

1 FL. OZ./30 ml ℮